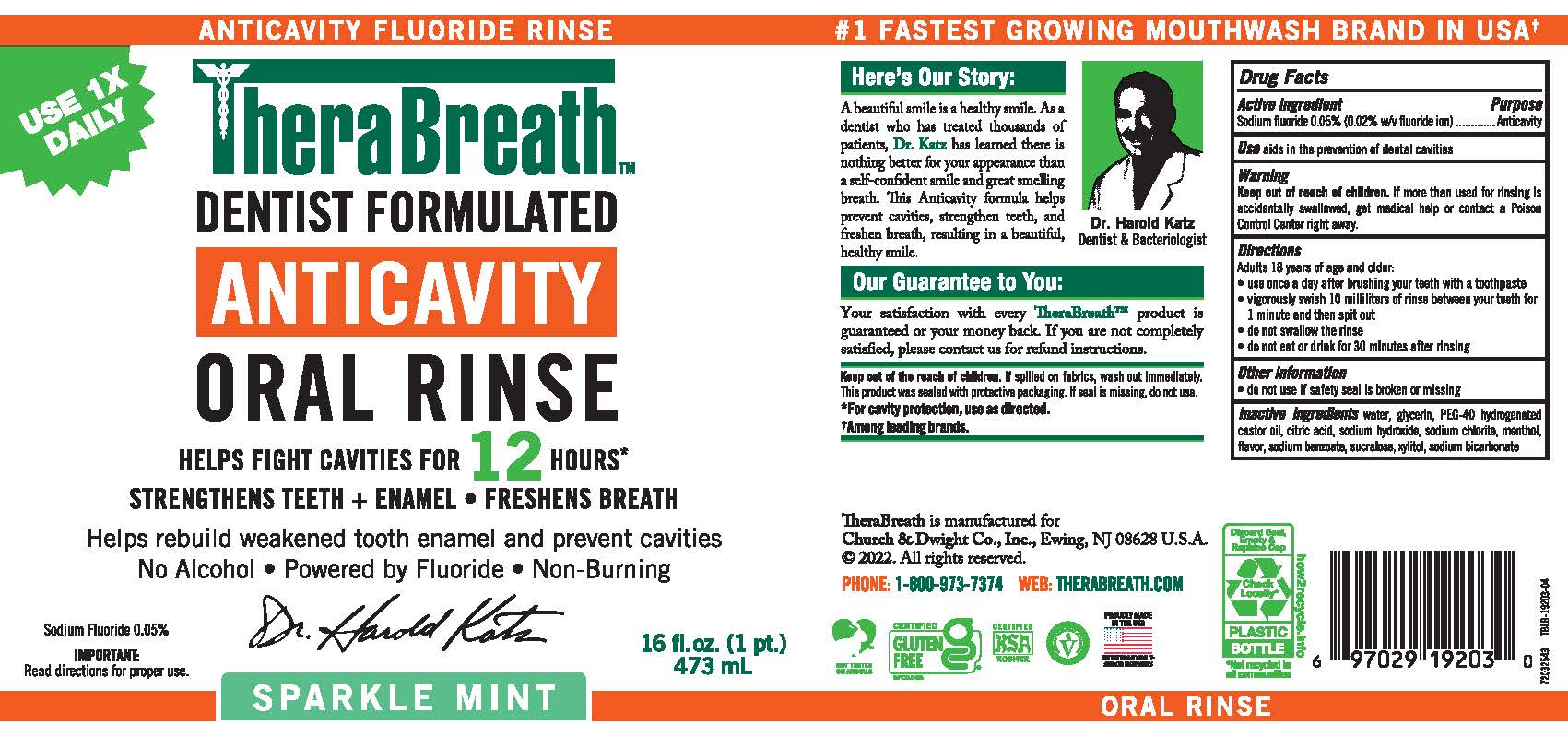 DRUG LABEL: Therabreath Anticavity
NDC: 10237-260 | Form: RINSE
Manufacturer: Church & Dwight Co., Inc.
Category: otc | Type: HUMAN OTC DRUG LABEL
Date: 20250528

ACTIVE INGREDIENTS: SODIUM FLUORIDE 0.005 mg/10 mL
INACTIVE INGREDIENTS: WATER; GLYCERIN; SODIUM BENZOATE; SODIUM HYDROXIDE; SODIUM CHLORITE; XYLITOL; CITRIC ACID MONOHYDRATE; SUCRALOSE; SODIUM CITRATE, UNSPECIFIED FORM

Therabreath™ Anticavity Oral Rinse Sparkle Mint 0.05

Drug Facts

Active Ingredients

Sodium Fluoride 0.05% (0.02% w/v fluoride ion)

Purpose

Anticavity

Use

Aids in the prevention of dental cavities

Warnings

KEEP OUT OF REACH OF CHILDREN

Keep out of the reach of children.If more than used for rinsing is accidentally swallowed, get medical help or contact a Poison Control Center right away.

Directions

Adults and Children 18 years of age or older:

- Use once a day after brushing your teeth with a toothpaste.
- Vigorously swish 10 milliliters of rinse between your teeth for 1 minute and then spit out.
- Do not swallow the rinse.
- Do not eat or drink for 30 minutes after rinsing.

Other information

Do not use if safety seal is broken or missing

Inactive Ingredients

Water, Glycerin, PEG-40 Hydrogenated Castor Oil, Citric Acid, Sodium Hydroxide, Sodium Chlorite, Menthol, Citrus Lemon Peel Oil, Mentha Piperita Oil, Sodium Benzoate, Sucralose, Xylitol, Sodium Bicarbonate.

PRINCIPAL DISPLAY PANEL - 473 mL Bottle Label

USE 1X DAILY

ANTICAVITY FLUORIDE RINSE

TheraBreath™
DENTIST FORMULATED
ANTICAVITY
ORAL RINSE

HELPS FIGHT CAVITIES FOR 12 HOURS*
STRENGTHENS TEETH + ENAMEL • FRESHENS BREATH

Helps rebuild weakened tooth enamel and prevent cavities

No Alcohol • Powered by Fluoride • Non-Burning

Sodium Fluoride 0.05%

IMPORTANT:
Read directions for proper use.

Dr. Harold Katz

16 fl.oz. (1 pt.)

473 mL

SPARKLE MINT